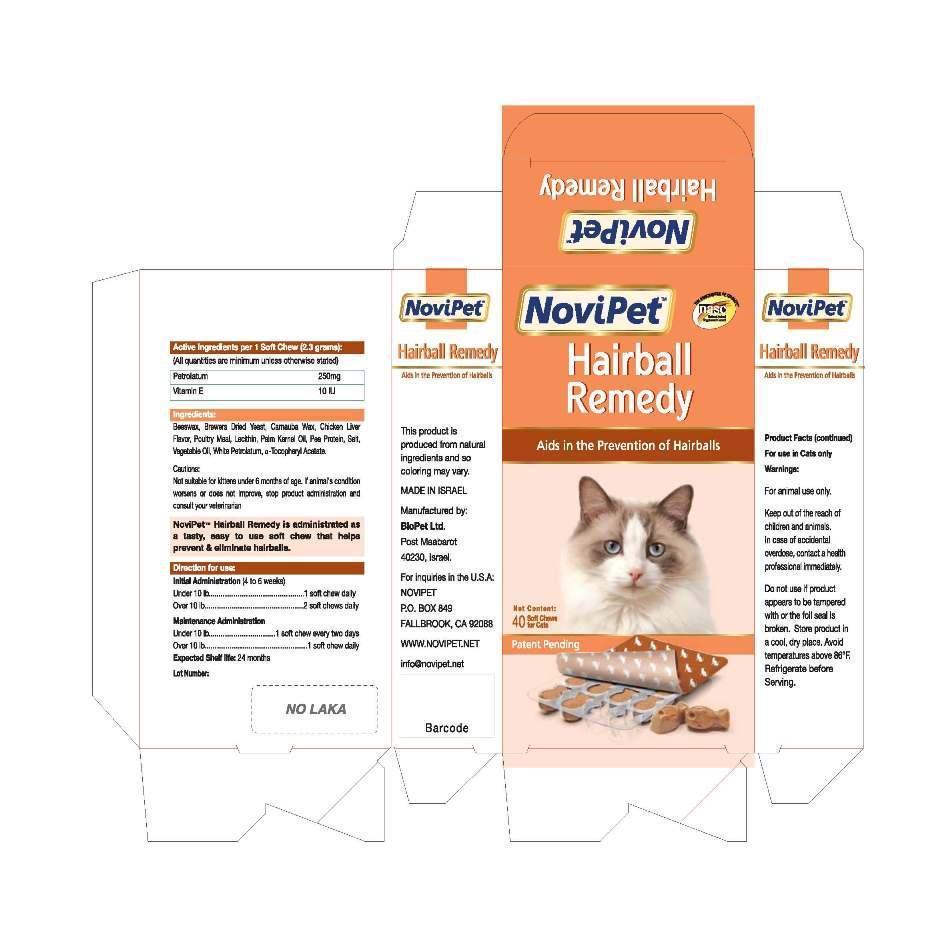 DRUG LABEL: Hairball Remedy
                
                
NDC: 45732-016 | Form: TABLET, CHEWABLE
Manufacturer: Novipet, Inc.
Category: animal | Type: OTC ANIMAL DRUG LABEL
Date: 20120914

ACTIVE INGREDIENTS: PETROLATUM 250 mg/1 1; TOCOPHEROL 10 [iU]/1 1

Novipet Hairball Remedy

CARTON FRONT PANEL

NoviPet

Hairball

Remedy

Aids in the Prevention of Hairballs

Net Contents: 40 Soft Chews for Cats

Patent Pending

CARTON LEFT SIDE PANEL

NoviPet Hairball Remedy

Aids in the Prevention of Hairballs

This product is
produced from natural
ingredients and so
coloring may vary.
MADE IN ISRAEL
Manufactured by:
BioPet Ltd.
Post Maabarot
40230, Israel
For inquiries in the U.S.A:
NOVIPET
P.O. BOX 849
FALLBROOK, CA 92088
WWW.NOVIPET.NET
info@novipet.net

CARTON RIGHT SIDE PANEL

NoviPet

Hairball Remedy

Aids in the Prevention of Hairballs

Product Facts (continued)
For use in cats only
warnings
For animal use only.
Keep out of the reach of
children and animals.
In case of accidental
overdose, contact a health
professional immediately.
Do not use if product
appears to be tampered
with or the foil seal is
broken. Store product in
a cool, dry place. Avoid
temperatures above 86^0F.
Refrigerate before
Serving.

ACTIVE INGREDIENT

Active Ingredients per 1 Soft Chew (2.3 grams):

(All quantities are minimum unless otherwise stated)
Petrolatum 250mg
Vitamin E 10 lU

INACTIVE INGREDIENT

Ingredients:
Beeswax, Brewers Dried Yeast, Carnuba Wax, Chicken Liver
Flavor, Poultry Meat, Lecithin, Palm Kernel Oil, Pea Protein, Salt,
Vegetable Oil, White PetroIatum, a-Tocopheryl Acetate.

PREGNANCY

Cautions:
Not suitable for kittens under 6 months of age. If animal's condition
worsens or does not improve, stop product administration and
consult your veterinarian

NoviPet- Hairball Remedy is administrated as
a tasty, easy to use soft chew that helps
prevent and eliminate halrballs

Directions for use:

Initial Administration (4 to 6 weeks)
Under 10 Ib .................................................. l soft chew daily

Over 10 Ib ................................................... 2 soft chews daily

Maintenance Administration
Under 10 Ib ................................... l soft chew every two days

Over 10 Ib ...................................................... l soft chew daily

Expected Shelf life: 24 months

Lot Number:

Do not use if product
appears to be tampered
with or the foil seal is
broken. Store product in
a cool, dry place. Avoid
temperatures above 86^0F.
Refrigerate before
Serving.

PACKAGE LABEL

Carton Labeling